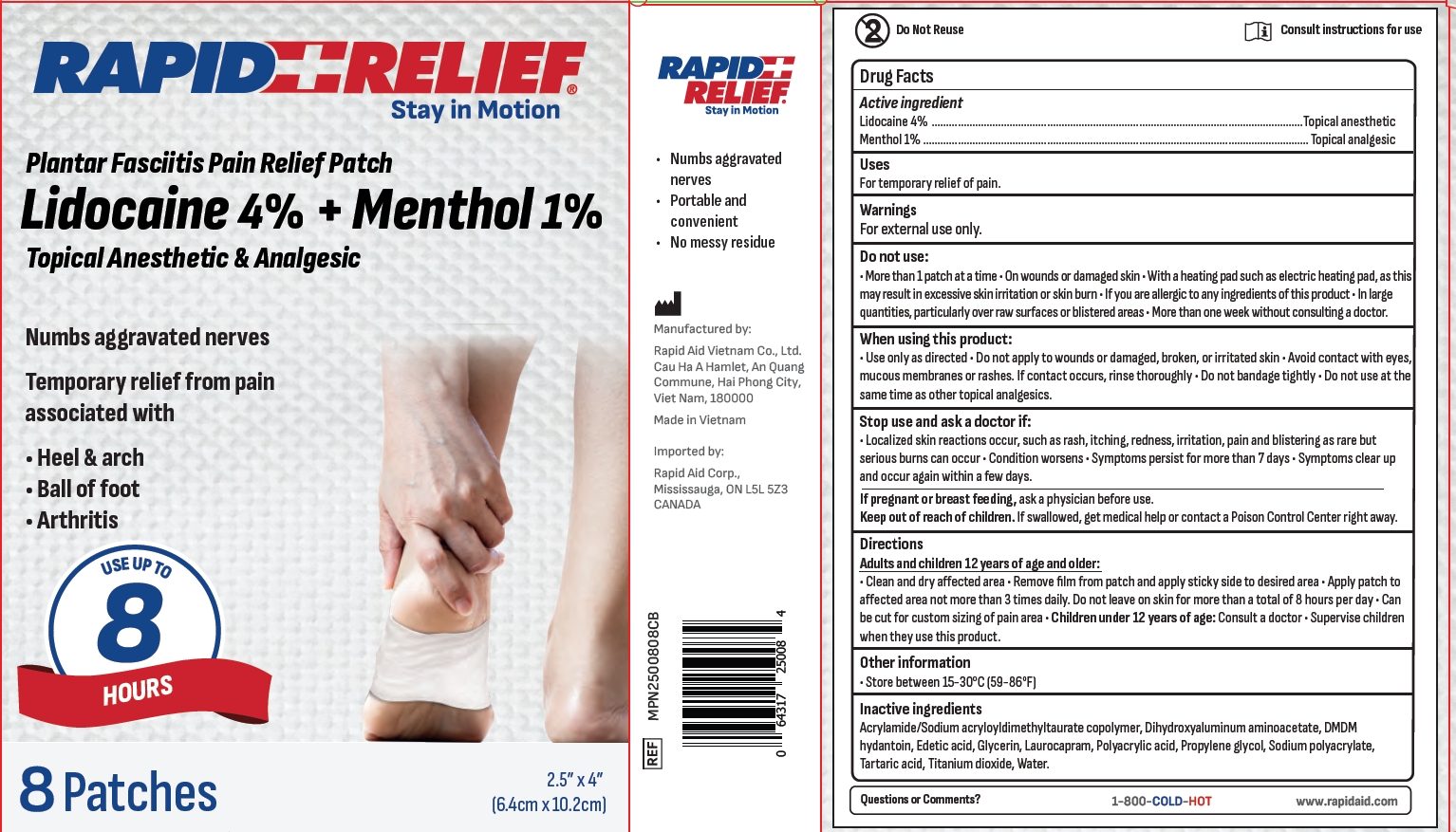 DRUG LABEL: Rapid Relief Plantar Fasciitis Pain Relief Patch
NDC: 83569-007 | Form: PATCH
Manufacturer: RAPID AID VIET NAM CO., LTD
Category: otc | Type: HUMAN OTC DRUG LABEL
Date: 20251016

ACTIVE INGREDIENTS: MENTHOL 1 g/100 g; LIDOCAINE 4 g/100 g
INACTIVE INGREDIENTS: POLYACRYLIC ACID (300000 MW); POLYACRYLIC ACID (800000 MW); DIHYDROXYALUMINUM AMINOACETATE; GLYCERIN; WATER; DMDM HYDANTOIN; EDETATE DISODIUM ANHYDROUS; SODIUM POLYACRYLATE (8000 MW); ACRYLAMIDE/SODIUM ACRYLOYLDIMETHYLTAURATE COPOLYMER (120000 MPA.S AT 1%); TARTARIC ACID; TITANIUM DIOXIDE; LAUROCAPRAM; PROPYLENE GLYCOL

Active Ingredient(s)

Lidocaine 4%
Menthol 1%

Purpose

Topical anesthetic

Topical analgesic

Use

For temporary relief of pain.

Warnings

For external use only.

Do not use

More than 1 patch at a time . On wounds or damaged skin . With a heating pad such as electric heating pad, as thismay result in excessive skin irritation or skin burn · lfyou are allergic to anyingredients of this product . ln largequantities, particularly over raw surfaces or blistered areas . More than one week without consulting a doctor.

When using this product:

Use only as directed . Do not apply to wounds or damaged, broken, or irritated skin · Avoid contact with eyesmucous membranes or rashes. lf contact occurs, rinse thoroughly · Do not bandage tightly. Do not use at thesame time as other topical analgesics.

Stop use and ask a doctor if:

. Localized skin reactions occur, such as rash, itching, redness, irritation, pain and blistering as rare butserious burns can occur . Condition worsens · Symptoms persist for more than 7 days · Symptoms clear upand occur again within a few days.

If pregnant or breast feeding, ask a physician before use.

KEEP OUT OF REACH OF CHILDREN

If swallowed, get medical help or contact a Poison Control Center right away.

Directions

Adults and children 12 years of age and older:Clean and dry affected area · Remove flm from patch and apply sticky side to desired area · Apply patch toaffected area not more than 3 times daily. Do not leave on skin for more than a total of8 hours per day. Canbe cut for custom sizing of pain area . Children under 12 years of age: Consult a doctor . Supervise childrenwhen they use this product.

STORAGE AND HANDLING

Store between 15-30℃(59-86℉)

Inactive ingredients

Acrylamide/Sodium acryloyldimethyltaurate copolymer, Dihydroxyaluminum aminoacetate, DMDMhydantoin, Edetic acid, Glycerin, Laurocapram, Polyacrylic acid, Propylene glycol, Sodium polyacrylateTartaric acid,Titanium dioxide. Water.